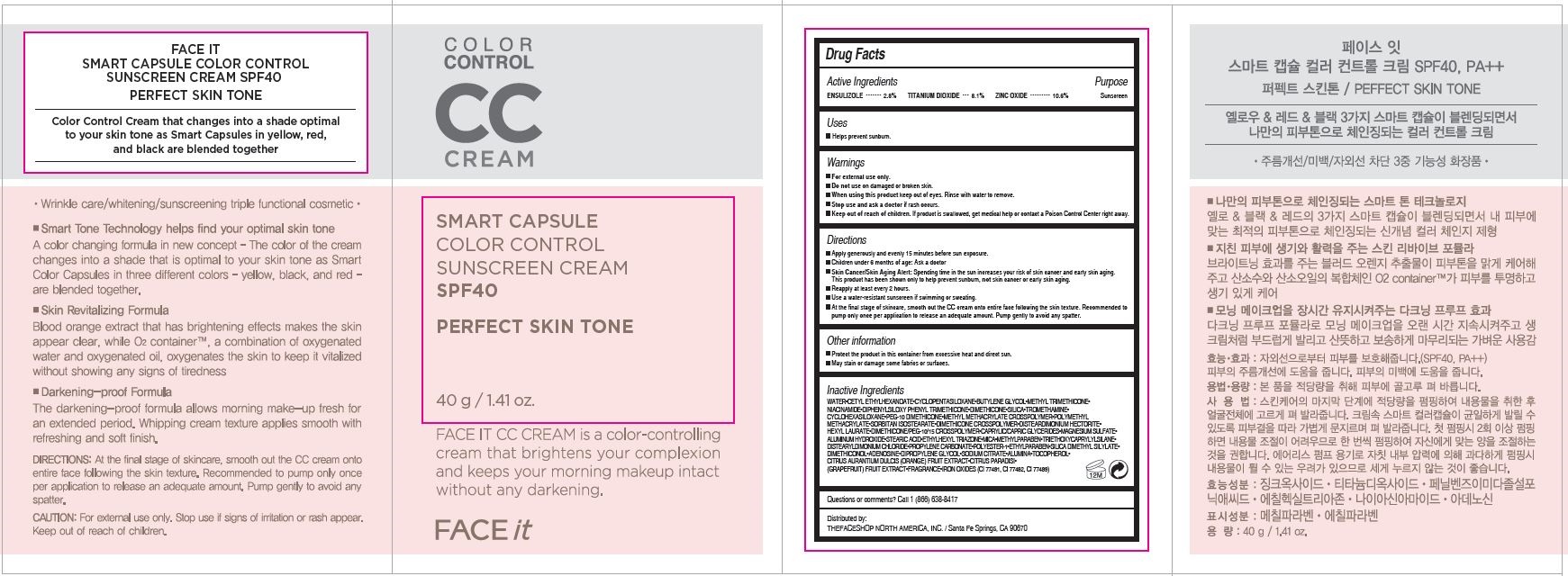 DRUG LABEL: FACE IT SMART COLOR CONTROL
NDC: 51523-661 | Form: CREAM
Manufacturer: THEFACESHOP CO., LTD.
Category: otc | Type: HUMAN OTC DRUG LABEL
Date: 20141120

ACTIVE INGREDIENTS: ZINC OXIDE 3.2 g/30 mL; ENSULIZOLE .8 g/30 mL; TITANIUM DIOXIDE 2.4 g/30 mL
INACTIVE INGREDIENTS: WATER

Face It Smart 32800661

Active Ingredients

ENSULIZOLE............. 2.8%
TITANIUM DIOXIDE.. 8.1%
ZINC OXIDE............. 10.6%

Purpose

Sunscreen

Sunscreen

Sunscreen

Warnings

For external use only.

Do not use on damaged or broken skin

When using this product keep out of eyes. Rinse with water to remove.

Stop use and ask a doctor if rash occurs.

Keep out of reach of children. If product is swallowed, get medical help or contact a Poison Control Center right away.

Directions

Apply generously and evenly 15 minutes before sun exposure.
Children under 6 months of age: Ask a doctor
Skin Cancer/Skin Aging Alert: Spending time in the sun increases your risk of skin cancer and early skin. aging. This product has been shown only to help prevent sunburn, not skin cancer or early skin aging.
Reapply at least every 2 hours
Use a water-resistant sunscreen if swimming or sweating.
At the final stage of skincare, smooth out the CC cream onto entire face following the skin texture.

Recommended to pump only once per application to release an adequate amount.

Pump gently to avoid any spatter.

Other Information

Protect the product in this container from excessive heat and direct sun

May stain or damage some fabrics or surfaces

Inactive Ingredients

WATER•CETYL ETHYLHEXANOATE•CYCLOPENTASILOXANE•BUTYLENE GLYCOL•METHYL TRIMETHICONE•
NIACINAMIDE•DIPHENYLSILOXY PHENYL TRIMETHICONE•DIMETHICONE•SILICA•TROMETHAMINE•
CYCLOHEXASILOXANE•PEG-10 DIMETHICONE•METHYL METHACRYLATE CROSSPOLYMER•POLYMETHYL
METHACRYLATE•SORBITAN ISOSTEARATE•DIMETHICONE CROSSPOLYMER•DISTEARDIMONIUM HECTORITE•
HEXYL LAURATE•DIMETHICONE/PEG-10/15 CROSSPOLYMER•CAPRYLIC/CAPRIC GLYCERIDES•MAGNESIUM SULFATE•
ALUMINUM HYDROXIDE•STEARIC ACID•ETHYLHEXYL TRIAZONE•MICA•METHYLPARABEN•TRIETHOXYCAPRYLYLSILANE•
DISTEARYLDIMONIUM CHLORIDE•PROPYLENE CARBONATE•POLYESTER-1•ETHYLPARABEN•SILICA DIMETHYL SILYLATE•
DIMETHICONOL•ADENOSINE•DIPROPYLENE GLYCOL•SODIUM CITRATE•ALUMINA•TOCOPHEROL•
CITRUS AURANTIUM DULCIS (ORANGE) FRUIT EXTRACT•CITRUS PARADISI•
(GRAPEFRUIT) FRUIT EXTRACT•FRAGRANCE•IRON OXIDES (CI 77491, CI 77492, CI 77499)

Questions or comments? Call 1 (866) 638-8417

Distributed by:

THEFACESHOP NORTH AMERICA, INC. / Santa Fe Springs, CA 90670

PACKAGE LABEL

COLOR CONTROLCC CREAM
SMART CAPSULE CONTROL
SUNSCREEN CREAM
SPF40

PERFECT SKIN TONE

FACE IT CC CREAM is a color-controlling cream that brightens your complexion
and keeps your morning makeup intact without any darkening.

FACE it